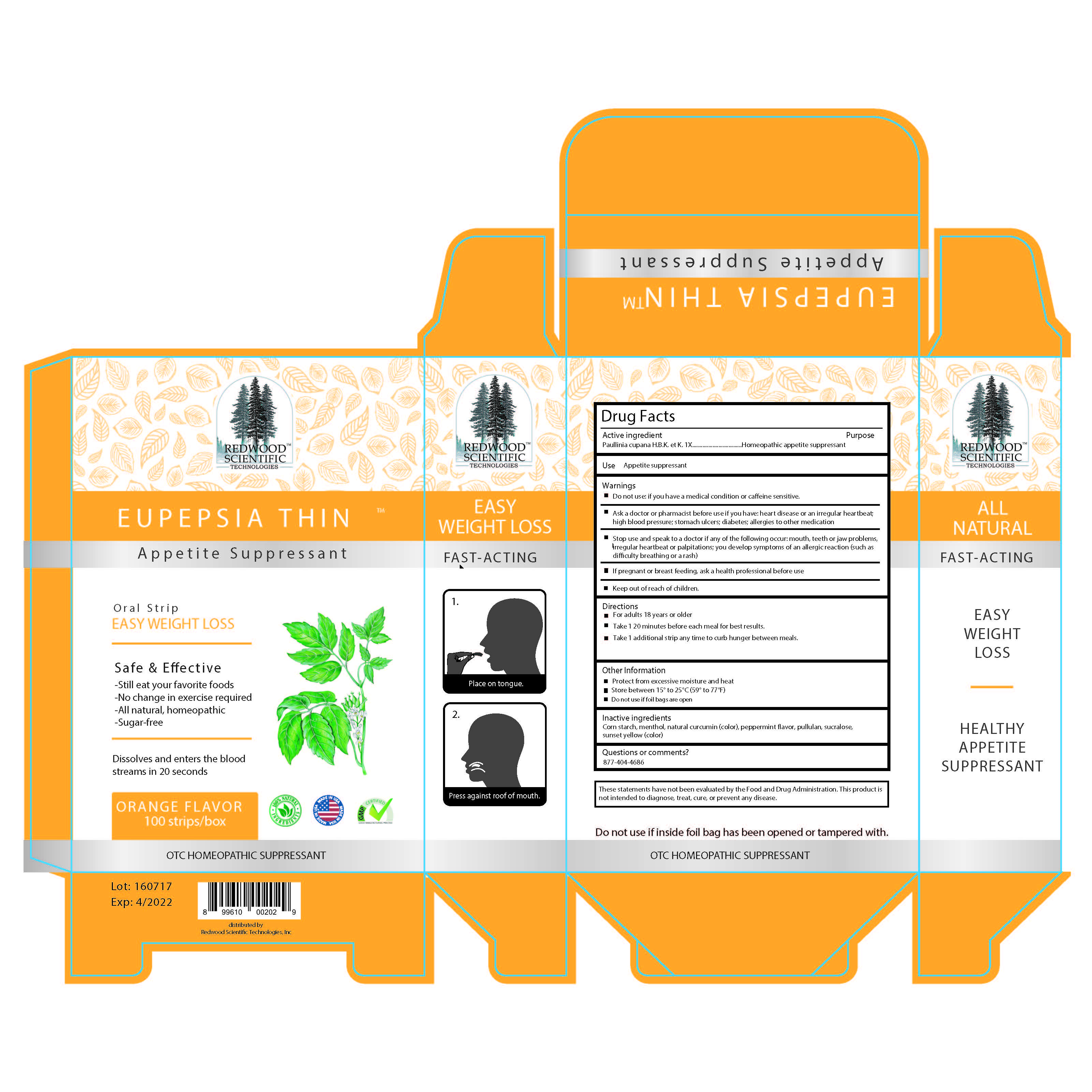 DRUG LABEL: Eupepsia Thin
NDC: 72041-000 | Form: STRIP
Manufacturer: Dalian Holyone Bio-Technologyco Ltd
Category: homeopathic | Type: HUMAN OTC DRUG LABEL
Date: 20180119

ACTIVE INGREDIENTS: PAULLINIA CUPANA SEED 1 [hp_X]/1 1
INACTIVE INGREDIENTS: STARCH, CORN; SUCRALOSE; PEPPERMINT; MENTHOL; PULLULAN

Eupepsia Thin

Active ingredient - Paulinia Cupana H.B.K et K

PURPOSE

Homeopathic appetite suppresant

DOSAGE AND ADMINISTRATION

Directions and Use

- For adults 18 years or older
- Take 1 strip when hunger strikes to suppress appetite between meals
- take 1 additional strip any time to curb hunger between meals
- Take 1 strip 20 minutes before meal for best results.

DO NOT USE IF -you have a medical condition or caffeine sensitive

Ask doctor of pharmacist before use if you have - heart disease or an irregular hearbeat; high blood pressure; stomach ulcers; diabetes; allergies to other medications

STOP USE AND SPEAK TO A DOCTOR IF - any of the following occur - mouth, teeth or jaw problems, irregular heartbeat or palpitations, you develop symptoms of an allergic reaction - such as difficulty breathing or a rash.

IF PREGNANT OR BREAST FEEDING - ask a health professional before use

Keep out of reach of children.

USE

Appetite suppresant

INACTIVE INGREDIENTS

Corn Starch, menthol, natural curcumin (color), peppermint flavor, pullulan, sucralose, sunset yellow (color)